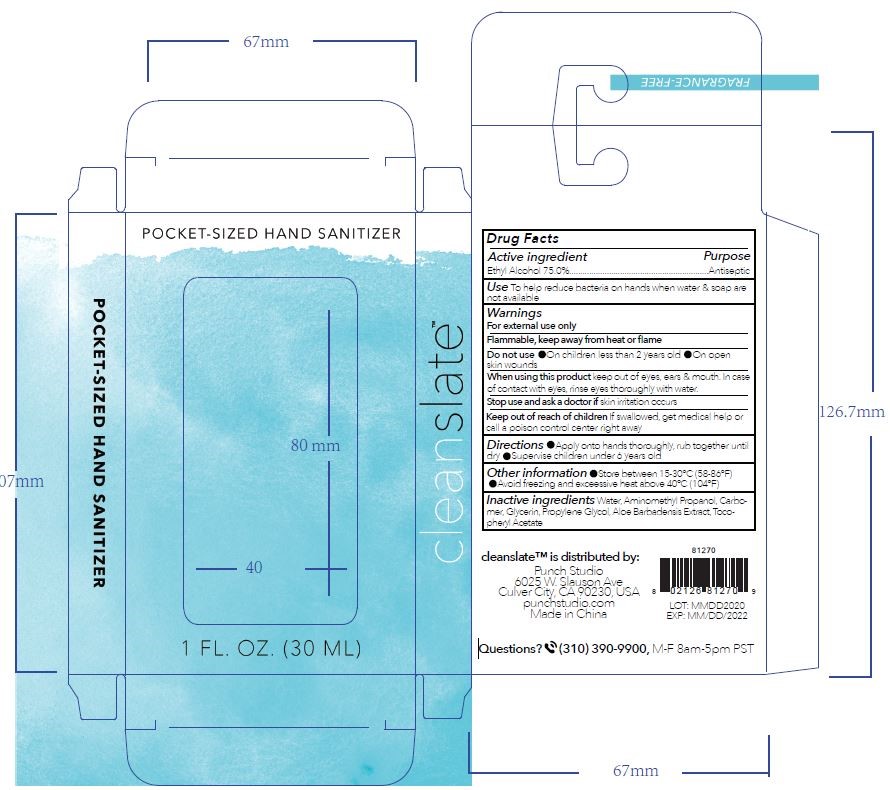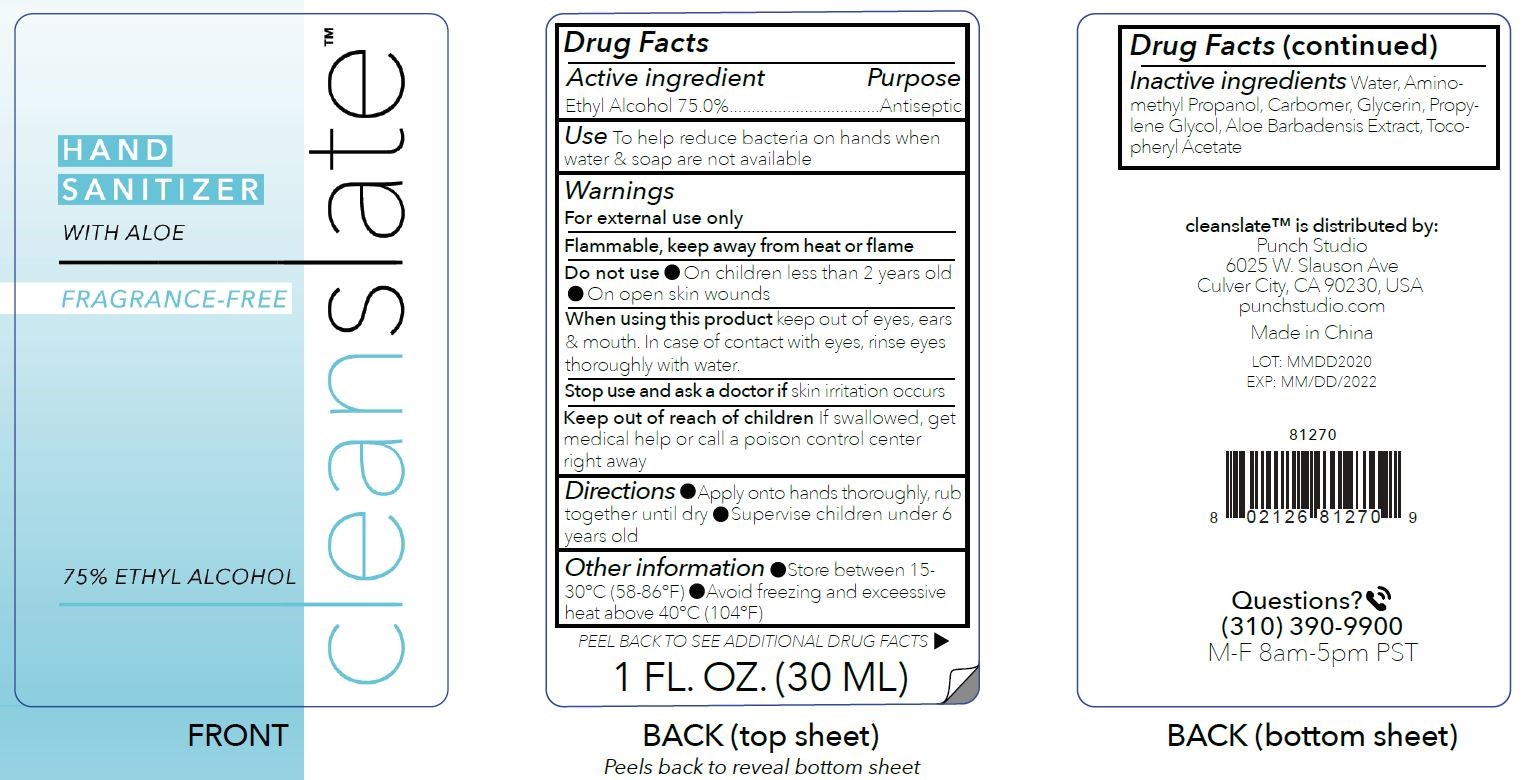 DRUG LABEL: Cleanslate
NDC: 75601-1003 | Form: LIQUID
Manufacturer: Punch Studio, LLC
Category: otc | Type: HUMAN OTC DRUG LABEL
Date: 20220112

ACTIVE INGREDIENTS: ALCOHOL 75 mL/100 mL
INACTIVE INGREDIENTS: GLYCERIN; CARBOMER HOMOPOLYMER, UNSPECIFIED TYPE; WATER; PROPYLENE GLYCOL; ALOE VERA LEAF; AMINOMETHYLPROPANOL; ALPHA-TOCOPHEROL ACETATE

Hand sanitizer

Active Ingredient(s)

Ethyl Alcohol 75% Purpose: Antiseptic

Purpose

Antiseptic

Use

To help reduce bacteria on hands when water & soap are not available

Warnings

For external use only

Flammable, keep away from heat or flame

Do not use

- On children less than 2 years old
- On open skin wounds

When using this product keep out of eyes, ears & mouth. In case of contact with eyes, rinse eyes thoroughly with water.

Stop use and ask a doctor if skin irritation occurs.

Keep out of reach of children If swallowed, get medical help or contact a poison control center right away

Directions

- Apply onto hands thoroughly, rub together until dry
- Supervise children under 6 years old

Other information

- Store between 15-30°C (59-86°F)
- Avoid freezing and excessive heat above 40°C (104°F)

Inactive ingredients

Water, Aminomethyl Propanol, Carbomer, Glycerin, Propylene Glycol, Aloe Barbadensis Extract, Tocopheryl Acetate

Package Label - Principal Display Panel

30 mL NDC: 75601-1270-1 30 mL NDC: 75601-1270-2